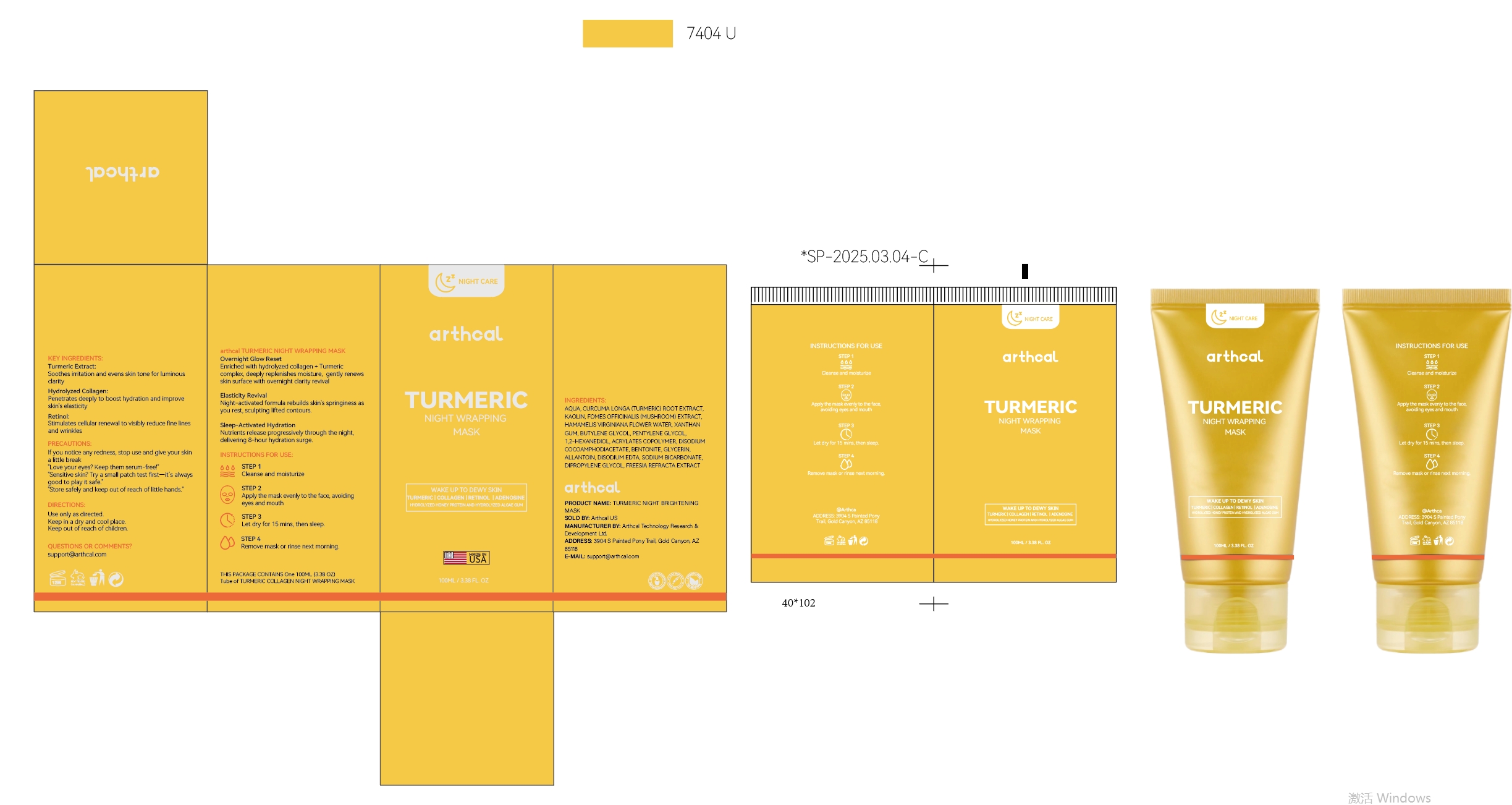 DRUG LABEL: Arthcal Turmeric Night Wrapping Mask
NDC: 85212-0015 | Form: LOTION
Manufacturer: Beijing JUNGE Technology Co., Ltd.
Category: otc | Type: HUMAN OTC DRUG LABEL
Date: 20250227

ACTIVE INGREDIENTS: HYDROLYZED PORCINE COLLAGEN (ENZYMATIC; 3000 MW) 5 g/100 mL; CURCUMA LONGA WHOLE 5 g/100 mL; KOJIC ACID 2 g/100 mL; ADENOSINE 0.1 g/100 mL
INACTIVE INGREDIENTS: DIPROPYLENE GLYCOL 5 mL/100 mL; POLYVINYL ALCOHOL 5 mL/100 mL; RETINOL 1 mL/100 mL; AQUA 66.4 mL/100 mL; MATRICARIA CHAMOMILLA 0.5 mL/100 mL; PROPOLIS CERA 1 mL/100 mL; ASCORBIC ACID 1 mL/100 mL; CALENDULA OFFICINALIS SEED OIL 0.5 mL/100 mL; HYDROXYETHYLCELLULOSE 0.1 mL/100 mL; HYDROLYZED ELASTIN 2 mL/100 mL; GLYCERETH-6 LAURATE 0.5 mL/100 mL; 1,2-HEXANEDIOL 2 mL/100 mL; ETHYLHEXYLGLYCERIN 0.1 mL/100 mL; OCTANEDIOL 0.1 mL/100 mL; ALOE BARBADENSIS LEAF 0.5 mL/100 mL; LAURYL GLUCOSIDE 1 mL/100 mL; SODIUM METAPHOSPHATE 0.1 mL/100 mL; PECTIN 0.5 mL/100 mL; SUCROSE 0.5 mL/100 mL; CELLULOSE GUM 0.1 mL/100 mL

DOSAGE AND ADMINISTRATION

100ml(3.38fl.oz)

INSTRUCTIONS FOR USE

1. Cleanse and moisturize.
2. Apply the mask evenly to the face, avoiding eyes and mouth.
3. Let dry for 15 mins, then sleep.

4. Remove mask or rinse next morning.

ACTIVE INGREDIENT

CURCUMA LONGA EXTRACT
HYDROLYZED COLLAGEN
KOJIC ACID
ADENOSINE

INACTIVE INGREDIENT

AQUA
DIPROPYLENE GLYCOL
POLYVINYL ALCOHOL
1,2-HEXANEDIOL
HYDROLYZED ELASTIN
RETINOL
ASCORBIC ACID
PROPOLIS EXTRACT
LAURYL GLUCOSIDE
Calendula officinalis
GLYCERETH-6 LAURATE
Aloe barbadensis miller
Matricaria chamomilla
PECTIN
SUCROSE
CELLULOSE GUM
HYDROXYETHYLCELLULOSE
SODIUM METAPHOSPHATE
OCTANEDIOL
ETHYLHEXYLGLYCERIN

PURPOSE

Deeply replenishes moisture, restores elasticity, and enhances skin firmness.

Keep out of reach of children.

WARNINGS

For External Use Only.
Avoid Direct Contact with Eyes.
If the product gets into your eyes, rinse immediately with plenty of water.
Discontinue Use if Irritation Occurs: If redness, itching, or irritation develops, stop use.
Do Not Apply on Broken or Irritated Skin.